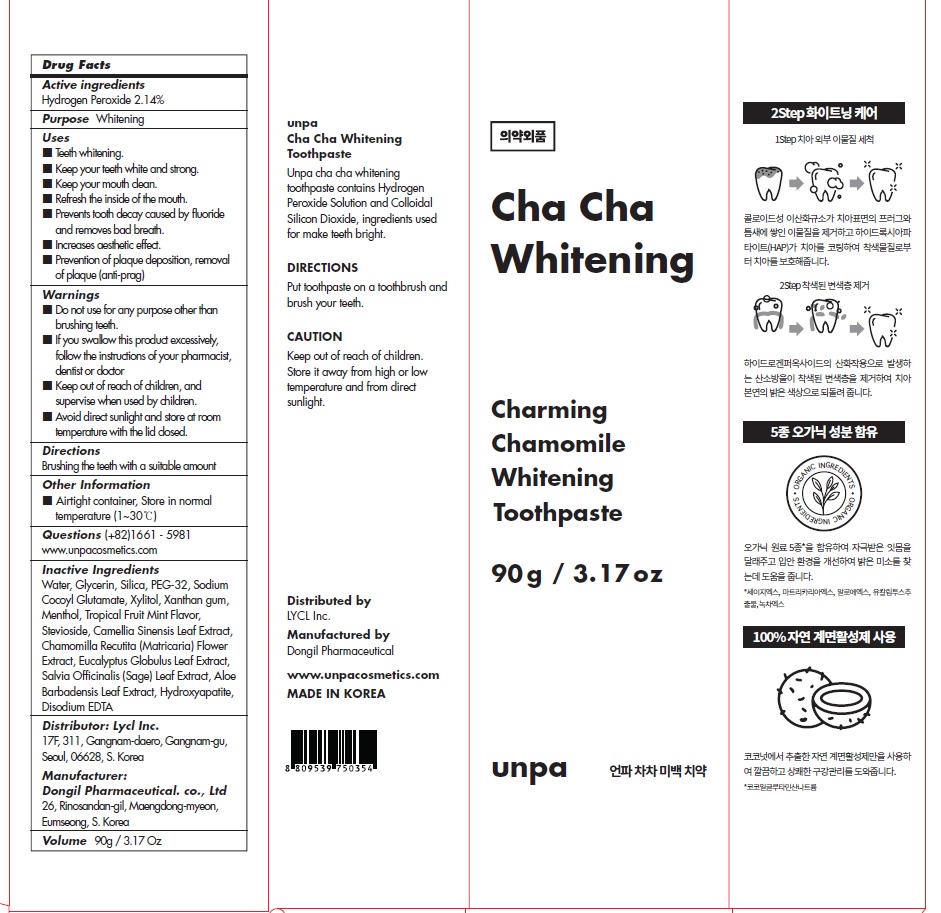 DRUG LABEL: Unpa Cha Cha Premium Whitening Toothpaste
NDC: 73134-060 | Form: PASTE, DENTIFRICE
Manufacturer: Lycl Inc.
Category: otc | Type: HUMAN OTC DRUG LABEL
Date: 20210311

ACTIVE INGREDIENTS: Hydrogen Peroxide 1.92 g/90 g
INACTIVE INGREDIENTS: Water; Glycerin; SILICON DIOXIDE

ACTIVE INGREDIENT

Hydrogen Peroxide 2.14%

INACTIVE INGREDIENTS

Water, Glycerin, Silica, PEG-32, Sodium Cocoyl Glutamate, Xylitol, Xanthan gum, Menthol, Tropical Fruit Mint Flavor, Stevioside, Camellia Sinensis Leaf Extract, Chamomilla Recutita (Matricaria) Flower Extract, Eucalyptus Globulus Leaf Extract, Salvia Officinalis (Sage) Leaf Extract, Aloe
Barbadensis Leaf Extract, Hydroxyapatite, Disodium EDTA

PURPOSE

Whitening

WARNINGS

■ Do not use for any purpose other than brushing teeth.
■ If you swallow this product excessively, follow the instructions of your pharmacist, dentist or doctor
■ Keep out of reach of children, and supervise when used by children.
■ Avoid direct sunlight and store at room temperature with the lid closed.

■ Keep out of reach of children, and supervise when used by children.

Uses

■ Teeth whitening.
■ Keep your teeth white and strong.
■ Keep your mouth clean.
■ Refresh the inside of the mouth.
■ Prevents tooth decay caused by fluoride and removes bad breath.
■ Increases aesthetic effect.
■ Prevention of plaque deposition, removal of plaque (anti-prag)

Directions

Brushing the teeth with a suitable amount

Other Information

■ Airtight container, Store in normal temperature (1~30℃)

QUESTIONS

(+82)1661 - 5981
www.unpacosmetics.com